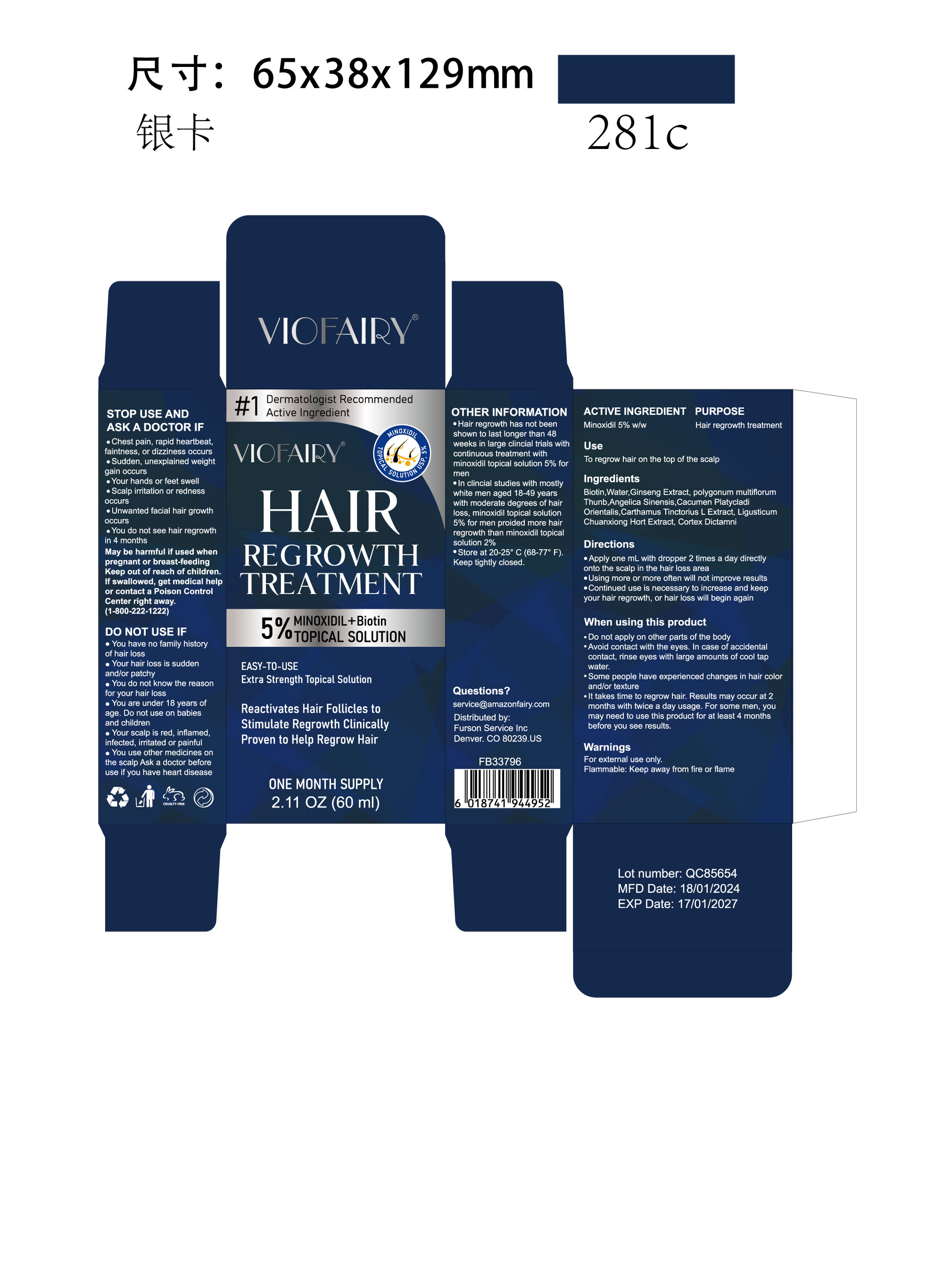 DRUG LABEL: VIOFAIRY 5% Minoxidil  Hair Growth oil
NDC: 83804-106 | Form: LIQUID
Manufacturer: Shenzhen Shandian Jingling Technology Co., Ltd.
Category: otc | Type: HUMAN OTC DRUG LABEL
Date: 20240314

ACTIVE INGREDIENTS: MINOXIDIL 5 g/100 mL
INACTIVE INGREDIENTS: LIGUSTICUM SINENSE SUBSP. CHUANXIONG ROOT; WATER; POLYGONATUM MULTIFLORUM ROOT; ANGELICA SINENSIS ROOT OIL; CORDIA DICHOTOMA WHOLE; SAFFLOWER; ASIAN GINSENG; BIOTIN; PLATYCLADUS ORIENTALIS LEAF

83804-106

Active Ingredient

Minoxidil 5%

Purpose

Hair Regrowth Treatment

Use

to regrow hair on the top of the scalp

Warnings

For external use only.
Flammable: Keep away from fire or flame

Do not use

• you have no family history of hair loss
• your hair loss is sudden and/or patchy
• you do not know the reason for your hair loss
• you are under 18 years of age. Do not use on babies and children
• your scalp is red, inflamed, infected, irritated or painful
• you use other medicines on the scalp

When Using

• do not apply on other parts of the body
• avoid contact with the eyes. In case of accidental contact, rinse eyes with large amounts of cool tap water.
• some people have experienced changes in hair color and/or texture
• it takes time to regrow hair. Results may occur at 2 months with twice a day usage. For some men, you may need to use this product for at least 4 months before you see results.

Stop Use

• chest pain, rapid heartbeat, faintness, or dizziness occurs
• sudden, unexplained weight gain occurs
• your hands or feet swell
• scalp irritation or redness occurs
• unwanted facial hair growth occurs
• you do not see hair regrowth in 4 months
May be harmful if used when pregnant or breast-feeding
Keep out of reach of children. If swallowed, get medical help or contact a Poison Control Center right away.(1-800-222-1222)

Ask Doctor

When Pregnant or breast-feeding

Keep Oot Of Reach Of Children

If swallowed, get medical help or contact a Poison Control Center right away. (1-800-222-1222)

Directions

• apply one mL with dropper 2 times a day directly onto the scalp in the hair loss area
• using more or more often will not improve results
• continued use is necessary to increase and keep your hair regrowth, or hair loss will begin again

Other information

• see hair loss pictures on side of this carton
• before use, read all information on carton and enclosed leaflet
• keep the carton. It contains important information.
• hair regrowth has not been shown to last longer than 48 weeks in large clincial trials with continuous treatment with minoxidil topical solution 5% for men
• in clincial studies with mostly white men aged 18-49 years with moderate degrees of hair loss, minoxidil topical solution 5% for men proided more hair regrowth than minoxidil topical solution 2%
• store at 20-25° C (68-77° F). Keep tightly closed.

Inactive ingredients

Biotin
Water
Ginseng Extroct
polygonum multiflorum Thunb
Angelica Sinensis
Cacumen Platycladi Orientalis
Carthamus Tinctorius L Extract
Ligusticum Chuanxiong Hort Extract
Cortex Dictamni

Questions

service@amazonfairy.com